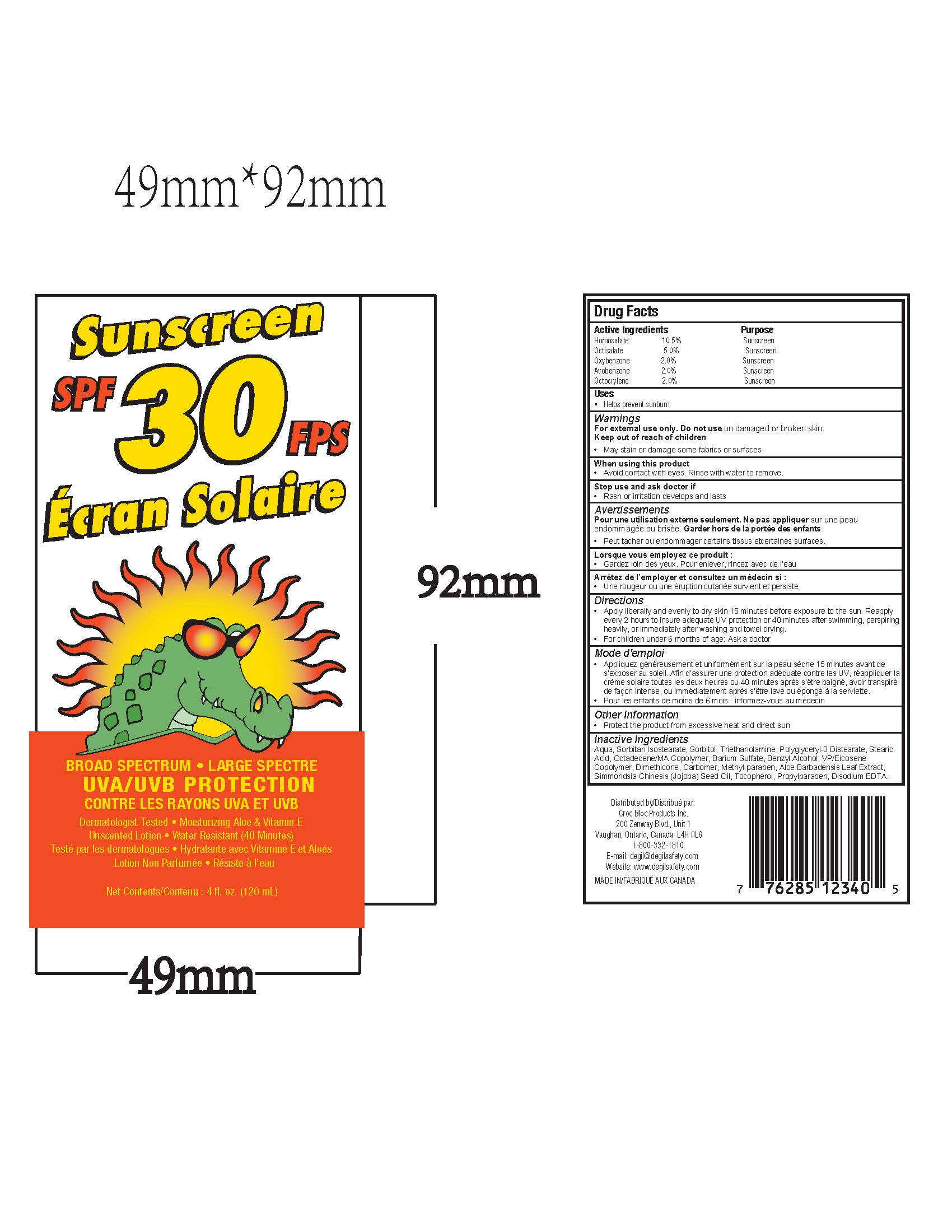 DRUG LABEL: Croc Bloc Broad Spectrum SPF 30 FPS Ecran Solaire
NDC: 58331-030 | Form: LOTION
Manufacturer: Degil Safety Products (1989) Inc.
Category: otc | Type: HUMAN OTC DRUG LABEL
Date: 20221121

ACTIVE INGREDIENTS: HOMOSALATE 10.5 g/100 mL; OCTISALATE 5 g/100 mL; OCTOCRYLENE 2 g/100 mL; OXYBENZONE 2 g/100 mL; AVOBENZONE 2 g/100 mL
INACTIVE INGREDIENTS: WATER; SORBITAN ISOSTEARATE; SORBITOL; TROLAMINE; POLYGLYCERYL-3 DISTEARATE; STEARIC ACID; BARIUM SULFATE; BENZYL ALCOHOL; DIMETHICONE; CARBOMER HOMOPOLYMER TYPE C (ALLYL PENTAERYTHRITOL CROSSLINKED); METHYLPARABEN; ALOE VERA LEAF; JOJOBA OIL; TOCOPHEROL; PROPYLPARABEN; EDETATE DISODIUM

Croc Bloc Broad Spectrum SPF 30 FPS Ecran Solaire

Drug Facts

ACTIVE INGREDIENT

PURPOSE

Active Ingredients |  | Purposes
Homosalate | 10.5% | Sunscreen
Octisalate | 5.0% | Sunscreen
Oxybenzone | 2.0% | Sunscreen
Avobenzone | 2.0% | Sunscreen
Octocrylene | 2.0% | Sunscreen

Warnings

For external use only

- Discontinue use if skin irritation develops or increases
- If irritation persists, consult a health care practitioner

WHEN USING

- Avoid contact with eyes
- If contact occurs, rinse thoroughly with water

ASK DOCTOR

- Consult a healthcare practitioner prior to use on children less than six months of age

WHEN USING

- May stain or damage some fabrics or surfaces

- Keep out of reach of children

Directions

Shake well. Apply generously 15-30 minutes prior to exposure to the sun. Reapply as needed or after swimming, towel drying, perspiring heavily, washing and vigorous activity.

Other Ingredients

Aqua, Sorbitan Isostearate, Sorbitol, Triethanolamine, Polyglyceryl-3 Distearate, Stearic Acid, Octadecene/MA Copolymer, Barium Sulfate, Benzyl Alcohol, VP/Eicosene Copolymer, Dimethicone, Carbomer, Methyl-paraben, Aloe Barbadensis Leaf Extract, Simmondsia Chinesis (Jojoba) Seed Oil, Tocopherol, Propylparaben, Disodium EDTA

PRINCIPAL DISPLAY PANEL - 120 mL Bottle Label

Sunscreen

SPF 30 FPS

Écran Solaire

BROAD SPECTRUM • LARGE SPECTRE
UVA/UVB PROTECTION

CONTRE LES RAYONS UVA ET UVB

Dermatologist Tested • Moisturizing Aloe & Vitamin E

Unscented Lotion • Water Sweat Resistant (40 Minutes)
Testé par les dermatologues • Hydratante avec Vitamine E et Aloés

Lotion Non Parfumée • Résiste à l'eau